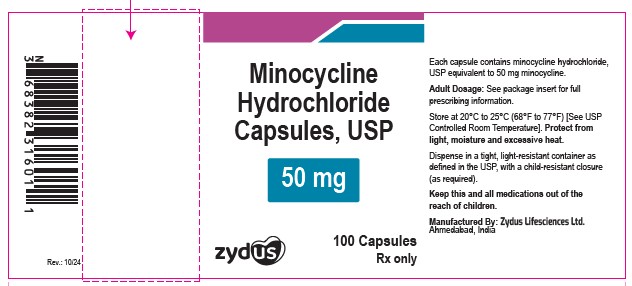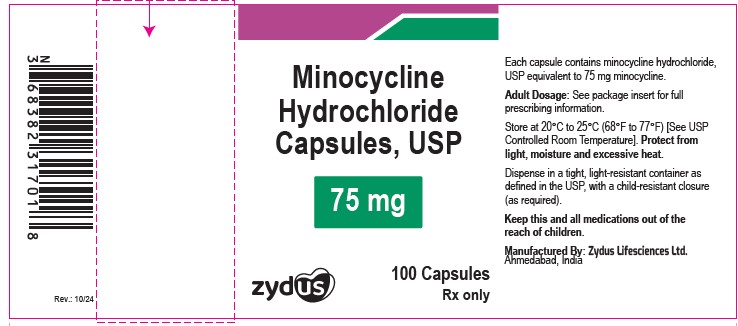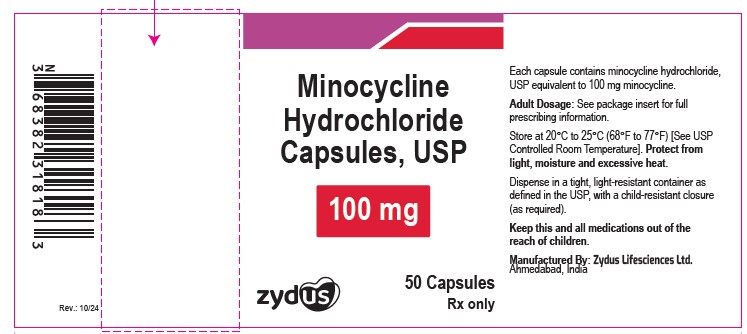 DRUG LABEL: Minocycline hydrochloride
NDC: 70771-1426 | Form: CAPSULE
Manufacturer: Zydus Lifesciences Limited
Category: prescription | Type: HUMAN PRESCRIPTION DRUG LABEL
Date: 20241003

ACTIVE INGREDIENTS: MINOCYCLINE HYDROCHLORIDE 50 mg/1 1
INACTIVE INGREDIENTS: STARCH, CORN; MAGNESIUM STEARATE; GELATIN; TITANIUM DIOXIDE; D&C RED NO. 33; FD&C RED NO. 3; FD&C YELLOW NO. 6; FERROSOFERRIC OXIDE; PROPYLENE GLYCOL; D&C YELLOW NO. 10; FD&C BLUE NO. 1; FD&C BLUE NO. 2; FD&C RED NO. 40; SHELLAC; AMMONIA; ALUMINUM OXIDE

Minocycline Hydrochloride Capsules, USP

PACKAGE LABEL.PRINCIPAL DISPLAY PANEL

NDC 70771-1426-1

Minocycline Hydrochloride Capsules USP, 50 mg

100 Capsules

Rx only

NDC 70771-1427-1

Minocycline Hydrochloride Capsules USP, 75 mg

100 Capsules

Rx only

NDC 70771-1428-7

Minocycline Hydrochloride Capsules USP, 100 mg

50 Capsules

Rx only